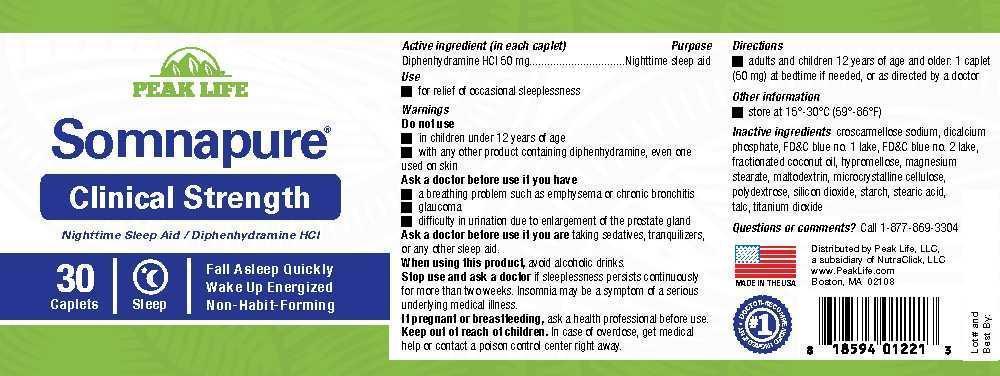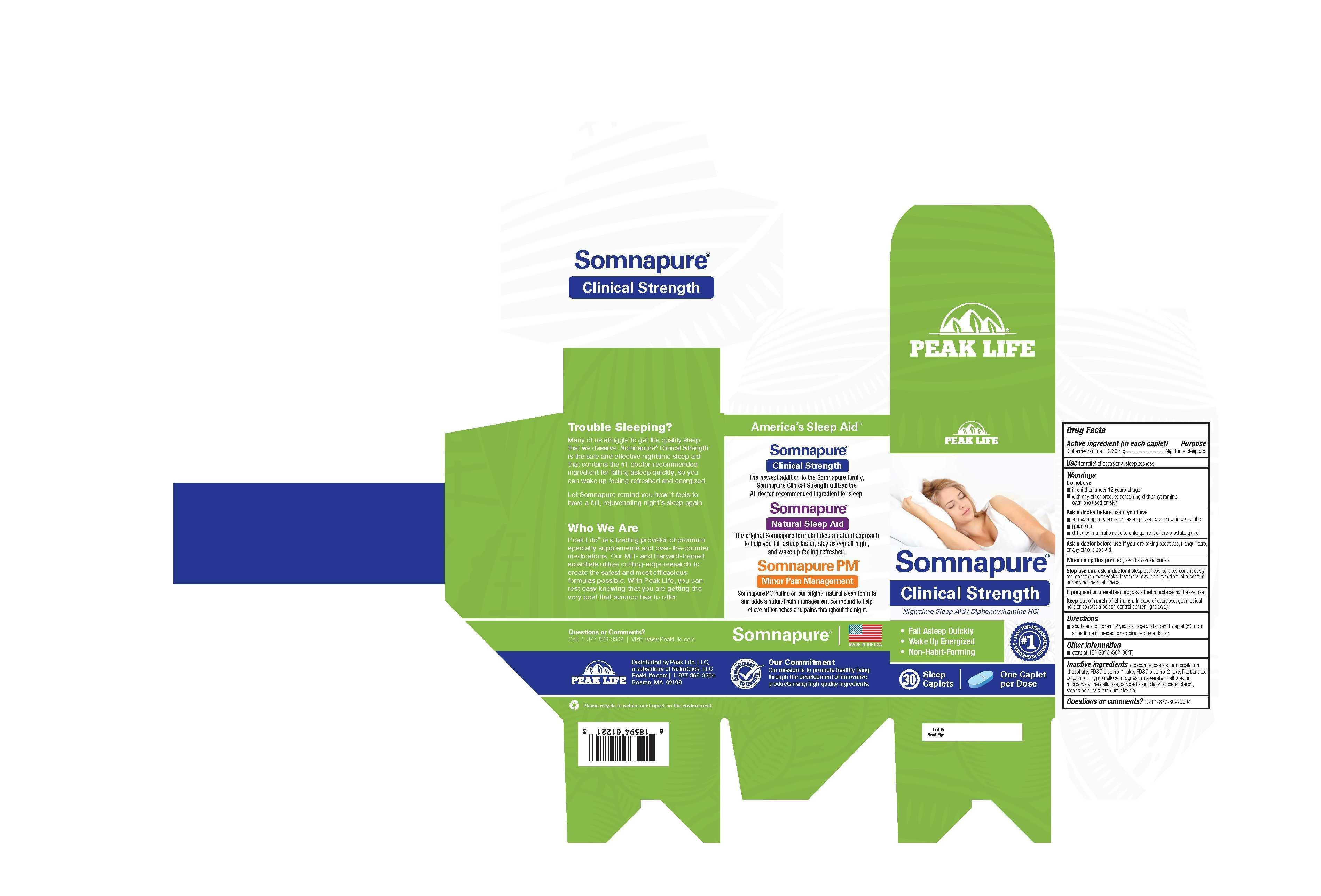 DRUG LABEL: Somnapure
NDC: 69721-001 | Form: TABLET, COATED
Manufacturer: NutraClick, LLC
Category: otc | Type: HUMAN OTC DRUG LABEL
Date: 20150409

ACTIVE INGREDIENTS: DIPHENHYDRAMINE HYDROCHLORIDE 50 mg/1 1
INACTIVE INGREDIENTS: CROSCARMELLOSE SODIUM; CALCIUM PHOSPHATE, DIBASIC, ANHYDROUS; FD&C BLUE NO. 1; FD&C BLUE NO. 2; medium-chain triglycerides; HYPROMELLOSES; MAGNESIUM STEARATE; MALTODEXTRIN; CELLULOSE, MICROCRYSTALLINE; POLYDEXTROSE; SILICON DIOXIDE; STARCH, CORN; STEARIC ACID; TALC; TITANIUM DIOXIDE

Somnapure Clinical Strength

Drug Facts

Active ingredient (in each caplet)

Diphenhydramine HCl 50 mg

Purpose

Nighttime sleep aid

INDICATIONS AND USAGE

Use for relief of occasional sleeplessness

Warnings

Do not use

- in children under 12 years of age
- with any other product containing diphenhydramine, even one used on skin

Ask a doctor before use if you have

- a breathing problem such as emphysema or chronic bronchitis
- glaucoma
- difficulty in urination due to enlargement of the prostate gland

Ask a doctor before use if you are taking sedatives, tranquilizers, or any other sleep aid.

When using this product, avoid alcoholic drinks.

Stop use and ask a doctor if sleeplessness persists continuously for more than two weeks. Insomnia may be a symptom of a serious underlying medical illness.

PREGNANCY OR BREAST FEEDING

If pregnant or breastfeeding, ask a health professional before use.

Keep out of reach of children. In case of overdose, get medical help or contact a poison control center right away.

Directions

- adults and children 12 years of age and older: 1 caplet (50 mg) at bedtime if needed, or as directed by a doctor

Other information

- store at 15°-30°C (59°-86°F)

INACTIVE INGREDIENT

Inactive ingredients croscarmellose sodium, dicalcium phosphate, FD&C blue no. 1 lake, FD&C blue no. 2 lake, fractionated coconut oil, hypromellose, magnesium stearate, maltodextrin, microcrystalline cellulose, polydextrose, silicon dioxide, starch, stearic acid, talc titanium dioxide

Questions or comments? Call 1-877-869-3304

PACKAGE LABEL

Peak Life

Somnapure®Clinical Strength

Nighttime Sleep Aid / Diphenhydramine HCL

- Fall Asleep Quickly
- Wake Up Energized
- Non-Habit-Forming

#1 Doctor-Recommended Ingredient

30 Sleep Caplets

One Caplet per Dose

Distributed by Peak Life, LLC,

a subsidiary of NutraClick, LLC

PeakLife.com / 1-877-869-3304

Boston, MA 02108